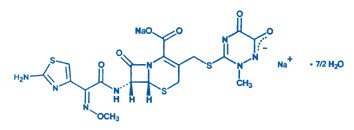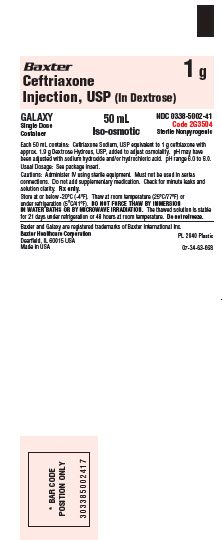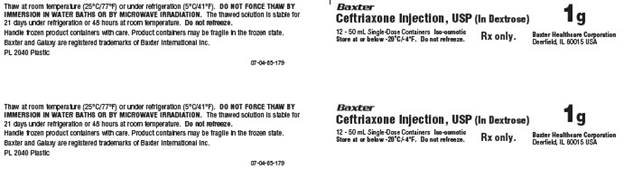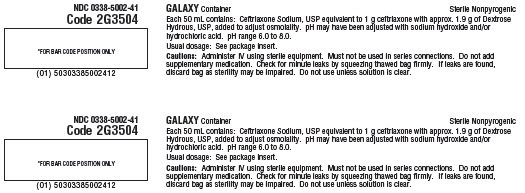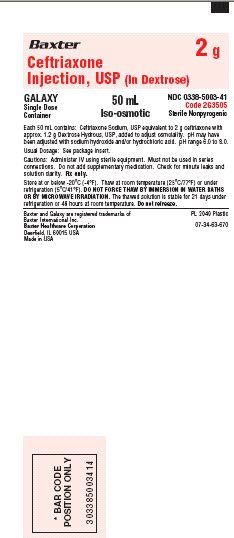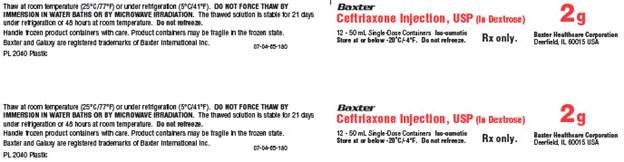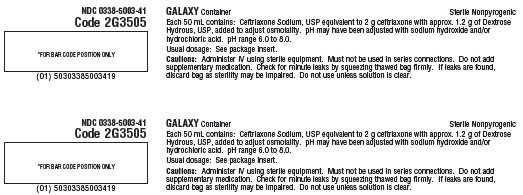 DRUG LABEL: Ceftriaxone
NDC: 0338-5002 | Form: INJECTION, SOLUTION
Manufacturer: Baxter Healthcare Company
Category: prescription | Type: HUMAN PRESCRIPTION DRUG LABEL
Date: 20241007

ACTIVE INGREDIENTS: CEFTRIAXONE SODIUM 1 g/50 mL
INACTIVE INGREDIENTS: DEXTROSE MONOHYDRATE 1.9 g/50 mL; SODIUM HYDROXIDE; HYDROCHLORIC ACID; WATER

Ceftriaxone Injection, USP (In Dextrose)
in Galaxy Container

Rx Only

To reduce the development of drug-resistant bacteria and maintain the effectiveness of Ceftriaxone Injection and other antibacterial drugs, Ceftriaxone Injection should be used only to treat or prevent infections that are proven or strongly suspected to be caused by bacteria.

DESCRIPTION

Ceftriaxone Injection, USP is a sterile, semisynthetic, broad-spectrum cephalosporin antibiotic for intravenous administration. Ceftriaxone sodium is (6R,7R)-7-[2-(2-Amino-4-thiazolyl)glyoxylamido]-8-oxo-3-[[(1,2,5,6-tetrahydro-2-methyl-5,6-dioxo-as-triazin-3-yl)thio]methyl]-5-thia-1-azabicyclo[4.2.0]oct-2-ene-2-carboxylic acid, 7²-(Z)-(O-methyloxime), disodium salt, sesquaterhydrate.

The chemical formula of ceftriaxone sodium is C18H16N8Na2O7S3•7/2 H2O. It has a calculated molecular weight of 661.60 and the following structural formula:

Ceftriaxone Sodium, USP is a white to yellowish-orange crystalline powder which is readily soluble in water, sparingly soluble in methanol and very slightly soluble in ethanol.

Ceftriaxone Injection, USP contains approximately 83 mg (3.6 mEq) of sodium per gram of ceftriaxone activity.

Ceftriaxone Injection, USP is supplied as a frozen, iso-osmotic, sterile, nonpyrogenic solution premixed in a dextrose diluent. Dextrose, USP has been added to adjust the osmolality (approximately 1.9 g and 1.2 g as dextrose hydrous to the 1 g and 2 g dosages, respectively). The pH may be adjusted with sodium hydroxide and/or hydrochloric acid. Solutions of premixed Ceftriaxone Injection, USP may range from light yellow to amber in color. After thawing, the solution is intended for intravenous use. The pH of thawed solutions may range from 6.0 to 8.0. See HOW SUPPLIED for package description.

The plastic container for the frozen solution is fabricated from a specially designed multilayer plastic. Solutions are in contact with the polyethylene layer of this container and can leach out certain chemical components of the plastic in very small amounts within the expiration period. The suitability of the plastic has been confirmed in tests in animals according to the USP biological tests for plastic containers as well as by tissue culture toxicity studies.

CLINICAL PHARMACOLOGY

Average plasma concentrations of ceftriaxone following a single 30-minute intravenous (IV) infusion of a 0.5, 1 or 2 gm dose in healthy subjects are presented in Table 1.

Table 1
Ceftriaxone Plasma Concentrations
After Single Dose Administration
Dose/Route | Average Plasma Concentrations (mcg/mL)
 | 0.5 hr | 1 hr | 2 hr | 4 hr | 6 hr | 8 hr | 12 hr | 16 hr | 24 hr
0.5 gm IV [IV doses were infused at a constant rate over 30 minutes.] | 82 | 59 | 48 | 37 | 29 | 23 | 15 | 10 | 5
1 gm IV | 151 | 111 | 88 | 67 | 53 | 43 | 28 | 18 | 9
2 gm IV | 257 | 192 | 154 | 117 | 89 | 74 | 46 | 31 | 15

Multiple IV doses ranging from 0.5 to 2 gm at 12- to 24-hour intervals resulted in 15% to 36% accumulation of ceftriaxone above single dose values.

Ceftriaxone concentrations in urine are shown in Table 2.

Table 2
Urinary Concentrations of Ceftriaxone
After Single Dose Administration
Dose/Route | Average Urinary Concentrations (mcg/mL)
 | 0-2 hr | 2-4 hr | 4-8 hr | 8-12 hr | 12-24 hr | 24-48 hr
0.5 gm IV | 526 | 366 | 142 | 87 | 70 | 15
1 gm IV | 995 | 855 | 293 | 147 | 132 | 32
2 gm IV | 2692 | 1976 | 757 | 274 | 198 | 40

Thirty-three percent to 67% of a ceftriaxone dose was excreted in the urine as unchanged drug and the remainder was secreted in the bile and ultimately found in the feces as microbiologically inactive compounds. After a 1 gm IV dose, average concentrations of ceftriaxone, determined from 1 to 3 hours after dosing, were 581 mcg/mL in the gallbladder bile, 788 mcg/mL in the common duct bile, 898 mcg/mL in the cystic duct bile, 78.2 mcg/gm in the gallbladder wall and 62.1 mcg/mL in the concurrent plasma.

Over a 0.15 to 3 gm dose range in healthy adult subjects, the values of elimination half-life ranged from 5.8 to 8.7 hours; apparent volume of distribution from 5.78 to 13.5 L; plasma clearance from 0.58 to 1.45 L/hour; and renal clearance from 0.32 to 0.73 L/hour. Ceftriaxone is reversibly bound to human plasma proteins, and the binding decreased from a value of 95% bound at plasma concentrations of <25 mcg/mL to a value of 85% bound at 300 mcg/mL. Ceftriaxone crosses the blood placenta barrier.

The average values of maximum plasma concentration, elimination half-life, plasma clearance and volume of distribution after a 50 mg/kg IV dose and after a 75 mg/kg IV dose in pediatric patients suffering from bacterial meningitis are shown in Table 3. Ceftriaxone penetrated the inflamed meninges of infants and pediatric patients; CSF concentrations after a 50 mg/kg IV dose and after a 75 mg/kg IV dose are also shown in Table 3.

Table 3
Average Pharmacokinetic Parameters
of Ceftriaxone in Pediatric Patients
With Meningitis
 | 50 mg/kg IV | 75 mg/kg IV
Maximum Plasma Concentrations (mcg/mL) | 216 | 275
Elimination Half-life (hr) | 4.6 | 4.3
Plasma Clearance (mL/hr/kg) | 49 | 60
Volume of Distribution (mL/kg) | 338 | 373
CSF Concentration - inflamed meninges (mcg/mL) | 5.6 | 6.4
Range (mcg/mL) | 1.3-18.5 | 1.3-44
Time after dose (hr) | 3.7 (± 1.6) | 3.3 (± 1.4)

Compared to that in healthy adult subjects, the pharmacokinetics of ceftriaxone were only minimally altered in elderly subjects and in patients with renal impairment or hepatic dysfunction (Table 4); therefore, dosage adjustments are not necessary for these patients with ceftriaxone dosages up to 2 gm per day. Ceftriaxone was not removed to any significant extent from the plasma by hemodialysis. In 6 of 26 dialysis patients, the elimination rate of ceftriaxone was markedly reduced.

Table 4
Average Pharmacokinetic Parameters
of Ceftriaxone in Humans
Subject Group | Elimination Half-life (hr) | Plasma Clearance (L/hr) | Volume of Distribution (L)
Healthy Subjects | 5.8-8.7 | 0.58-1.45 | 5.8-13.5
Elderly Subjects (mean age, 70.5 yr) | 8.9 | 0.83 | 10.7
Patients With Renal Impairment
Hemodialysis Patients (0-5 mL/min) [Creatinine clearance.] | 14.7 | 0.65 | 13.7
Severe (5-15 mL/min) | 15.7 | 0.56 | 12.5
Moderate (16-30 mL/min) | 11.4 | 0.72 | 11.8
Mild (31-60 mL/min) | 12.4 | 0.70 | 13.3
Patients With Liver Disease | 8.8 | 1.1 | 13.6

The elimination of ceftriaxone is not altered when Ceftriaxone Injection is co-administered with probenecid.

Interaction with Calcium

Two in vitro studies, one using adult plasma and the other neonatal plasma from umbilical cord blood, have been carried out to assess interaction of ceftriaxone and calcium. Ceftriaxone concentrations up to 1 mM (in excess of concentrations achieved in vivo following administration of 2 grams ceftriaxone infused over 30 minutes) were used in combination with calcium concentrations up to 12 mM (48 mg/dL). Recovery of ceftriaxone from plasma was reduced with calcium concentrations of 6 mM (24 mg/dL) or higher in adult plasma or 4 mM (16 mg/dL) or higher in neonatal plasma. This may be reflective of ceftriaxone-calcium precipitation.

Microbiology

The bactericidal activity of ceftriaxone results from inhibition of cell wall synthesis. Ceftriaxone has a high degree of stability in the presence of beta-lactamases, both penicillinases and cephalosporinases, of gram-negative and gram-positive bacteria.

In an in vitro study antagonistic effects have been observed with the combination of chloramphenicol and ceftriaxone.

Ceftriaxone has been shown to be active against most strains of the following microorganisms, both in vitro and in clinical infections described in the INDICATIONS AND USAGE section.

Aerobic gram-negative microorganisms:

Acinetobacter calcoaceticus

Enterobacter aerogenes

Enterobacter cloacae

Escherichia coli

Haemophilus influenzae (including ampicillin-resistant and beta-lactamase producing strains)

Haemophilus parainfluenzae

Klebsiella oxytoca

Klebsiella pneumoniae

Moraxella catarrhalis (including beta-lactamase producing strains)

Morganella morganii

Neisseria gonorrhoeae (including penicillinase- and nonpenicillinase-producing strains)

Neisseria meningitidis

Proteus mirabilis

Proteus vulgaris

Serratia marcescens

Ceftriaxone is also active against many strains of Pseudomonas aeruginosa.

NOTE: Many strains of the above organisms that are resistant to multiple antibiotics, e.g., penicillins, cephalosporins, and aminoglycosides, are susceptible to ceftriaxone.

Aerobic gram-positive microorganisms:

Staphylococcus aureus (including penicillinase-producing strains)

Staphylococcus epidermidis

Streptococcus pneumoniae

Streptococcus pyogenes

Viridans group streptococci

NOTE: Methicillin-resistant staphylococci are resistant to cephalosporins, including ceftriaxone. Most strains of Group D streptococci and enterococci, e.g., Enterococcus (Streptococcus) faecalis, are resistant.

Anaerobic microorganisms:

Bacteroides fragilis

Clostridium species

Peptostreptococcus species

NOTE: Most strains of Clostridioides difficile are resistant.

The following in vitro data are available, but their clinical significance is unknown. Ceftriaxone exhibits in vitro minimal inhibitory concentrations (MICs) of ≤1 mcg/mL or less against most strains of the following microorganisms, however, the safety and effectiveness of ceftriaxone in treating clinical infections due to these microorganisms have not been established in adequate and well-controlled clinical trials.

Aerobic gram-negative microorganisms:

Citrobacter diversus

Citrobacter freundii

Providencia species (including Providencia rettgeri)

Salmonella species (including Salmonella typhi)

Shigella species

Aerobic gram-positive microorganisms:

Streptococcus agalactiae

Anaerobic microorganisms:

Prevotella (Bacteroides) bivius

Porphyromonas (Bacteroides) melaninogenicus

Susceptibility Tests

For specific information regarding susceptibility test interpretive criteria and associated test methods and quality control standards recognized by FDA for this drug, please see: http://www.fda.gov/STIC.

INDICATIONS AND USAGE

Before instituting treatment with Ceftriaxone Injection, appropriate specimens should be obtained for isolation of the causative organism and for determination of its susceptibility to the drug. Therapy may be instituted prior to obtaining results of susceptibility testing.

To reduce the development of drug-resistant bacteria and maintain the effectiveness of Ceftriaxone Injection and other antibacterial drugs, Ceftriaxone Injection should be used only to treat or prevent infections that are proven or strongly suspected to be caused by susceptible bacteria. When culture and susceptibility information are available, they should be considered in selecting or modifying antibacterial therapy. In the absence of such data, local epidemiology and susceptibility patterns may contribute to the empiric selection of therapy.

Ceftriaxone Injection is indicated for the treatment of the following infections when caused by susceptible organisms:

LOWER RESPIRATORY TRACT INFECTIONS caused by Streptococcus pneumoniae, Staphylococcus aureus, Haemophilus influenzae, Haemophilus parainfluenzae, Klebsiella pneumoniae, Escherichia coli, Enterobacter aerogenes, Proteus mirabilis or Serratia marcescens.

ACUTE BACTERIAL OTITIS MEDIA caused by Streptococcus pneumoniae, Haemophilus influenzae (including beta-lactamase producing strains) or Moraxella catarrhalis (including beta-lactamase producing strains).

NOTE: In one study lower clinical cure rates were observed with a single dose of ceftriaxone compared to 10 days of oral therapy. In a second study comparable cure rates were observed between single dose ceftriaxone and the comparator. The potentially lower clinical cure rate of ceftriaxone should be balanced against the potential advantages of parenteral therapy.

SKIN AND SKIN STRUCTURE INFECTIONS caused by Staphylococcus aureus, Staphylococcus epidermidis, Streptococcus pyogenes, Viridans group streptococci, Escherichia coli, Enterobacter cloacae, Klebsiella oxytoca, Klebsiella pneumoniae, Proteus mirabilis, Morganella morganii,* Pseudomonas aeruginosa, Serratia marcescens, Acinetobacter calcoaceticus, Bacteroides fragilis* or Peptostreptococcus species.

URINARY TRACT INFECTIONS (complicated and uncomplicated) caused by Escherichia coli, Proteus mirabilis, Proteus vulgaris, Morganella morganii or Klebsiella pneumoniae.

UNCOMPLICATED GONORRHEA (cervical/urethral and rectal) caused by Neisseria gonorrhoeae, including both penicillinase-and nonpenicillinase-producing strains, and pharyngeal gonorrhea caused by nonpenicillinase-producing strains of Neisseria gonorrhoeae.

PELVIC INFLAMMATORY DISEASE caused by Neisseria gonorrhoeae. Ceftriaxone, like other cephalosporins, has no activity against Chlamydia trachomatis. Therefore, when cephalosporins are used in the treatment of patients with pelvic inflammatory disease and Chlamydia trachomatis is one of the suspected pathogens, appropriate antichlamydial coverage should be added.

BACTERIAL SEPTICEMIA caused by Staphylococcus aureus, Streptococcus pneumoniae, Escherichia coli, Haemophilus influenzae or Klebsiella pneumoniae.

BONE AND JOINT INFECTIONS caused by Staphylococcus aureus, Streptococcus pneumoniae, Escherichia coli, Proteus mirabilis, Klebsiella pneumoniae or Enterobacter species.

INTRA-ABDOMINAL INFECTIONS caused by Escherichia coli, Klebsiella pneumoniae, Bacteroides fragilis, Clostridium species (Note: most strains of Clostridioides difficile are resistant) or Peptostreptococcus species.

MENINGITIS caused by Haemophilus influenzae, Neisseria meningitidis or Streptococcus pneumoniae. Ceftriaxone has also been used successfully in a limited number of cases of meningitis and shunt infection caused by Staphylococcus epidermidis* and Escherichia coli.*

*Efficacy for this organism in this organ system was studied in fewer than ten infections.

SURGICAL PROPHYLAXIS: The preoperative administration of a single 1 gm dose of ceftriaxone may reduce the incidence of postoperative infections in patients undergoing surgical procedures classified as contaminated or potentially contaminated (e.g., vaginal or abdominal hysterectomy or cholecystectomy for chronic calculous cholecystitis in high-risk patients, such as those over 70 years of age, with acute cholecystitis not requiring therapeutic antimicrobials, obstructive jaundice or common duct bile stones) and in surgical patients for whom infection at the operative site would present serious risk (e.g., during coronary artery bypass surgery). Although ceftriaxone has been shown to have been as effective as cefazolin in the prevention of infection following coronary artery bypass surgery, no placebo-controlled trials have been conducted to evaluate any cephalosporin antibiotic in the prevention of infection following coronary artery bypass surgery.

When administered prior to surgical procedures for which it is indicated, a single 1 gm dose of ceftriaxone provides protection from most infections due to susceptible organisms throughout the course of the procedure.

CONTRAINDICATIONS

Ceftriaxone Injection is contraindicated in patients with known allergy to the cephalosporin class of antibiotics. Solutions containing dextrose may be contraindicated in patients with known allergy to corn or corn products.

Neonates (≤28 days)

Hyperbilirubinemic neonates, especially prematures, should not be treated with Ceftriaxone Injection. In vitro studies have shown that ceftriaxone can displace bilirubin from its binding to serum albumin, leading to a possible risk of bilirubin encephalopathy in these patients.

Ceftriaxone Injection is contraindicated in neonates if they require (or are expected to require) treatment with calcium-containing IV solutions, including continuous calcium-containing infusions such as parenteral nutrition because of the risk of precipitation of ceftriaxone-calcium (see CLINICAL PHARMACOLOGY, WARNINGS and DOSAGE AND ADMINISTRATION).

A small number of cases of fatal outcomes in which a crystalline material was observed in the lungs and kidneys at autopsy have been reported in neonates receiving ceftriaxone and calcium-containing fluids. In some of these cases, the same intravenous infusion line was used for both ceftriaxone and calcium-containing fluids and in some a precipitate was observed in the intravenous infusion line. At least one fatality has been reported in a neonate in whom ceftriaxone and calcium-containing fluids were administered at different time points via different intravenous lines; no crystalline material was observed at autopsy in this neonate. There have been no similar reports in patients other than neonates.

WARNINGS

Hypersensitivity

BEFORE THERAPY WITH CEFTRIAXONE INJECTION IS INSTITUTED, CAREFUL INQUIRY SHOULD BE MADE TO DETERMINE WHETHER THE PATIENT HAS HAD PREVIOUS HYPERSENSITIVITY REACTIONS TO CEPHALOSPORINS, PENICILLINS OR OTHER DRUGS. THIS PRODUCT SHOULD BE GIVEN CAUTIOUSLY TO PENICILLIN-SENSITIVE PATIENTS. ANTIBIOTICS SHOULD BE ADMINISTERED WITH CAUTION TO ANY PATIENT WHO HAS DEMONSTRATED SOME FORM OF ALLERGY, PARTICULARLY TO DRUGS. SERIOUS ACUTE HYPERSENSITIVITY REACTIONS MAY REQUIRE THE USE OF SUBCUTANEOUS EPINEPHRINE AND OTHER EMERGENCY MEASURES.

As with other cephalosporins, anaphylactic reactions with fatal outcome have been reported, even if a patient is not known to be allergic or previously exposed.

Interaction with Calcium-Containing Products

Do not further dilute ceftriaxone injection with products containing calcium, such as Ringer’s solution or Hartmann’s solution, because a precipitate can form. Precipitation of ceftriaxone-calcium can also occur when ceftriaxone is mixed with calcium-containing solutions in the same IV administration line. Ceftriaxone must not be administered simultaneously with calcium-containing IV solutions, including continuous calcium-containing infusions such as parenteral nutrition via a Y-site. However, in patients other than neonates, ceftriaxone and calcium-containing solutions may be administered sequentially of one another if the infusion lines are thoroughly flushed between infusions with a compatible fluid. In vitro studies using adult and neonatal plasma from umbilical cord blood demonstrated that neonates have an increased risk of precipitation of ceftriaxone-calcium (see CLINICAL PHARMACOLOGY, CONTRAINDICATIONS and DOSAGE AND ADMINISTRATION).

Neurological Adverse Reactions

Serious neurological adverse reactions have been reported during postmarketing surveillance with ceftriaxone use. These reactions include encephalopathy (disturbance of consciousness including somnolence, lethargy, and confusion), seizures, myoclonus, and non-convulsive status epilepticus (see ADVERSE REACTIONS). Some cases occurred in patients with severe renal impairment who did not receive appropriate dosage adjustment. However, in other cases, neurological adverse reactions occurred in patients receiving an appropriate dosage adjustment. The neurological adverse reactions were reversible and resolved after discontinuation. If neurological adverse reactions associated with Ceftriaxone Injection therapy occur, discontinue Ceftriaxone Injection and institute appropriate supportive measures. Make appropriate dosage adjustments in patients with severe renal impairment (see DOSAGE AND ADMINISTRATION).

Clostridioides difficile

Clostridioides difficile associated diarrhea (CDAD) has been reported with use of nearly all antibacterial agents, including Ceftriaxone Injection, and may range in severity from mild diarrhea to fatal colitis. Treatment with antibacterial agents alters the normal flora of the colon leading to overgrowth of C. difficile.

C. difficile produces toxins A and B which contribute to the development of CDAD. Hypertoxin producing strains of C. difficile cause increased morbidity and mortality, as these infections can be refractory to antimicrobial therapy and may require colectomy. CDAD must be considered in all patients who present with diarrhea following antibiotic use. Careful medical history is necessary since CDAD has been reported to occur over two months after the administration of antibacterial agents.

If CDAD is suspected or confirmed, ongoing antibiotic use not directed against C. difficile may need to be discontinued. Appropriate fluid and electrolyte management, protein supplementation, antibiotic treatment of C. difficile, and surgical evaluation should be instituted as clinically indicated.

Hemolytic Anemia

An immune mediated hemolytic anemia has been observed in patients receiving cephalosporin class antibacterials including ceftriaxone. Severe cases of hemolytic anemia, including fatalities, have been reported during treatment in both adults and children. If a patient develops anemia while on ceftriaxone, the diagnosis of a cephalosporin associated anemia should be considered and ceftriaxone stopped until the etiology is determined.

PRECAUTIONS

General

Prescribing Ceftriaxone Injection in the absence of a proven or strongly suspected bacterial infection or a prophylactic indication is unlikely to provide benefit to the patient and increases the risk of the development of drug-resistant bacteria.

Although transient elevations of BUN and serum creatinine have been observed, at the recommended dosages, the nephrotoxic potential of Ceftriaxone Injection is similar to that of other cephalosporins.

Ceftriaxone is excreted via both biliary and renal excretion (see CLINICAL PHARMACOLOGY). Therefore, patients with mild to moderate renal impairment normally require no adjustment in dosage when usual doses of Ceftriaxone Injection are administered.

Dosage adjustments should not be necessary in patients with hepatic dysfunction; however, in patients with both hepatic dysfunction and significant renal disease, caution should be exercised and the Ceftriaxone Injection dosage should not exceed 2 gm daily.

Ceftriaxone has been associated with a fall in prothrombin activity. Those at risk include patients with renal or hepatic impairment or poor nutritional state, as well as patients receiving a protracted course of antimicrobial therapy, and patients previously stabilized on anticoagulant therapy. Prothrombin time should be monitored in patients at risk and exogenous vitamin K administered as indicated.

Prolonged use of Ceftriaxone Injection may result in overgrowth of nonsusceptible organisms. Careful observation of the patient is essential. If superinfection occurs during therapy, appropriate measures should be taken.

Ceftriaxone Injection should be prescribed with caution in individuals with a history of gastrointestinal disease, especially colitis.

There have been reports of sonographic abnormalities in the gallbladder of patients treated with ceftriaxone; some of these patients also had symptoms of gallbladder disease. These abnormalities appear on sonography as an echo without acoustical shadowing suggesting sludge or as an echo with acoustical shadowing which may be misinterpreted as gallstones. The chemical nature of the sonographically detected material has been determined to be predominantly a ceftriaxone-calcium salt. The condition appears to be transient and reversible upon discontinuation of ceftriaxone and institution of conservative management. Therefore, Ceftriaxone Injection should be discontinued in patients who develop signs and symptoms suggestive of gallbladder disease and/or the sonographic findings described above.

Cases of pancreatitis, possibly secondary to biliary obstruction, have been reported rarely in patients treated with ceftriaxone. Most patients presented with risk factors for biliary stasis and biliary sludge (preceding major therapy, severe illness, total parenteral nutrition). A cofactor role of ceftriaxone related biliary precipitation cannot be ruled out.

Information for Patients

Advise patients that neurological adverse reactions could occur with Ceftriaxone Injection use. Instruct patients or their caregivers to inform their healthcare provider at once of any neurological signs and symptoms, including encephalopathy (disturbance of consciousness including somnolence, lethargy, and confusion), seizures, myoclonus, and nonconvulsive status epilepticus, for immediate treatment, or discontinuation of Ceftriaxone Injection (see WARNINGS AND PRECAUTIONS).

Patients should be counseled that antibacterial drugs including Ceftriaxone Injection should only be used to treat bacterial infections. They do not treat viral infections (e.g., the common cold). When Ceftriaxone Injection is prescribed to treat a bacterial infection, patients should be told that although it is common to feel better early in the course of therapy, the medication should be taken exactly as directed. Skipping doses or not completing the full course of therapy may (1) decrease the effectiveness of the immediate treatment and (2) increase the likelihood that bacteria will develop resistance and will not be treatable by Ceftriaxone Injection or other antibacterial drugs in the future.

Diarrhea is a common problem caused by antibiotics which usually ends when the antibiotic is discontinued. Sometimes after starting treatment with antibiotics, patients can develop watery and bloody stools (with or without stomach cramps and fever) even as late as two or more months after having taken the last dose of the antibiotic. If this occurs, patients should contact their physician as soon as possible.

Carcinogenesis, Mutagenesis, Impairment of Fertility

Carcinogenesis

Considering the maximum duration of treatment and the class of the compound, carcinogenicity studies with ceftriaxone in animals have not been performed. The maximum duration of animal toxicity studies was 6 months.

Mutagenesis

Genetic toxicology tests included the Ames test, a micronucleus test and a test for chromosomal aberrations in human lymphocytes cultured in vitro with ceftriaxone. Ceftriaxone showed no potential for mutagenic activity in these studies.

Impairment of Fertility

Ceftriaxone produced no impairment of fertility when given intravenously to rats at daily doses up to 586 mg/kg/day, approximately 20 times the recommended clinical dose of 2 gm/day.

Pregnancy

Teratogenic Effects

Reproductive studies have been performed in mice and rats at doses up to 20 times the usual human dose and have no evidence of embryotoxicity, fetotoxicity or teratogenicity. In primates, no embryotoxicity or teratogenicity was demonstrated at a dose approximately 3 times the human dose.

There are, however, no adequate and well-controlled studies in pregnant women. Because animal reproductive studies are not always predictive of human response, this drug should be used during pregnancy only if clearly needed.

Nonteratogenic Effects

In rats, in the Segment I (fertility and general reproduction) and Segment III (perinatal and postnatal) studies with intravenously administered ceftriaxone, no adverse effects were noted on various reproductive parameters during gestation and lactation, including postnatal growth, functional behavior and reproductive ability of the offspring, at doses of 586 mg/kg/day or less.

Nursing Mothers

Low concentrations of ceftriaxone are excreted in human milk. Caution should be exercised when Ceftriaxone Injection is administered to a nursing woman.

Pediatric Use

Safety and effectiveness of Ceftriaxone Injection in neonates, infants and pediatric patients have been established for the dosages described in the DOSAGE AND ADMINISTRATION section. In vitro studies have shown that ceftriaxone, like some other cephalosporins, can displace bilirubin from serum albumin. Ceftriaxone Injection should not be administered to hyperbilirubinemic neonates, especially prematures (see CONTRAINDICATIONS).

Geriatric Use

Of the total number of subjects in clinical studies of ceftriaxone, 32% were 60 and over. No overall differences in safety or effectiveness were observed between these subjects and younger subjects, and other reported clinical experience has not identified differences in responses between the elderly and younger patients, but greater sensitivity of some older individuals cannot be ruled out.

The pharmacokinetics of ceftriaxone were only minimally altered in geriatric patients compared to healthy adult subjects and dosage adjustments are not necessary for geriatric patients with ceftriaxone dosages up to 2 grams per day (see CLINICAL PHARMACOLOGY).

ADVERSE REACTIONS

Ceftriaxone is generally well tolerated. In clinical trials, the following adverse reactions, which were considered to be related to ceftriaxone therapy or of uncertain etiology, were observed:

LOCAL REACTIONS — pain, induration and tenderness was 1% overall. Phlebitis was reported in <1% after IV administration.

HYPERSENSITIVITY — rash (1.7%). Less frequently reported (<1%) were pruritus, fever or chills.

HEMATOLOGIC — eosinophilia (6%), thrombocytosis (5.1%) and leukopenia (2.1%). Less frequently reported (<1%) were anemia, hemolytic anemia, neutropenia, lymphopenia, thrombocytopenia and prolongation of the prothrombin time.

GASTROINTESTINAL — diarrhea (2.7%). Less frequently reported (<1%) were nausea or vomiting, and dysgeusia. The onset of pseudomembranous colitis symptoms may occur during or after antibacterial treatment (see WARNINGS).

HEPATIC — elevations of SGOT (3.1%) or SGPT (3.3%). Less frequently reported (<1%) were elevations of alkaline phosphatase and bilirubin.

RENAL — elevations of the BUN (1.2%). Less frequently reported (<1%) were elevations of creatinine and the presence of casts in the urine.

CENTRAL NERVOUS SYSTEM — headache or dizziness were reported occasionally (<1%).

GENITOURINARY — moniliasis or vaginitis were reported occasionally (<1%).

MISCELLANEOUS — diaphoresis and flushing were reported occasionally (<1%).

Other rarely observed adverse reactions (<0.1%) include abdominal pain, agranulocytosis, allergic pneumonitis, anaphylaxis, basophilia, biliary lithiasis, bronchospasm, colitis, dyspepsia, epistaxis, flatulence, gallbladder sludge, glycosuria, hematuria, jaundice, leukocytosis, lymphocytosis, monocytosis, nephrolithiasis, palpitations, a decrease in the prothrombin time, renal precipitations, seizures, and serum sickness.

Postmarketing Experience

In addition to the adverse reactions reported during clinical trials, the following adverse experiences have been reported during clinical practice in patients treated with ceftriaxone. Data are generally insufficient to allow an estimate of incidence or to establish causation.

A small number of cases of fatal outcomes in which a crystalline material was observed in the lungs and kidneys at autopsy have been reported in neonates receiving ceftriaxone and calcium-containing fluids. In some of these cases, the same intravenous infusion line was used for both ceftriaxone and calcium-containing fluids and in some a precipitate was observed in the intravenous infusion line. At least one fatality has been reported in a neonate in whom ceftriaxone and calcium-containing fluids were administered at different time points via different intravenous lines; no crystalline material was observed at autopsy in this neonate. There have been no similar reports in patients other than neonates.

IMMUNE SYSTEM DISORDER – Acute myocardial ischemia with or without myocardial infarction may occur as part of an allergic reaction.

GASTROINTESTINAL – stomatitis and glossitis.

GENITOURINARY – oliguria.

DERMATOLOGIC – exanthema, allergic dermatitis, urticaria, edema. As with many medications, isolated cases of severe cutaneous adverse reactions (erythema multiforme, Stevens-Johnson syndrome or Lyell’s syndrome/toxic epidermal necrolysis) have been reported.

NEUROLOGIC – Encephalopathy, seizures, myoclonus, and non-convulsive status epilepticus (see WARNINGS AND PRECAUTIONS).

Cephalosporin Class Adverse Reactions

In addition to the adverse reactions listed above which have been observed in patients treated with ceftriaxone, the following adverse reactions and altered laboratory test results have been reported for cephalosporin class antibiotics:

Adverse Reactions

Allergic reactions, drug fever, serum sickness-like reaction, renal dysfunction, toxic nephropathy, reversible hyperactivity, hypertonia, hepatic dysfunction including cholestasis, aplastic anemia, hemorrhage, fall in prothrombin activity, and superinfection.

Altered Laboratory Tests

Positive direct Coombs’ test, false-positive test for urinary glucose, and elevated LDH.

Several cephalosporins have been implicated in triggering seizures, particularly in patients with renal impairment when the dosage was not reduced (see DOSAGE AND ADMINISTRATION). If seizures associated with drug therapy occur, the drug should be discontinued. Anticonvulsant therapy can be given if clinically indicated.

OVERDOSAGE

Ceftriaxone overdosage has been reported in patients with severe renal impairment. Reactions have included neurological outcomes, including encephalopathy, seizures, myoclonus, and non-convulsive status epilepticus. In the event of overdosage, discontinue Ceftriaxone Injection therapy and provide general supportive treatment (see DOSAGE AND ADMINISTRATION and WARNINGS AND PRECAUTIONS).

In the case of overdosage, drug concentration would not be reduced by hemodialysis or peritoneal dialysis. There is no specific antidote. Treatment of overdosage should be symptomatic.

DOSAGE AND ADMINISTRATION

Ceftriaxone Injection is administered intravenously.

Do not further dilute ceftriaxone injection with products containing calcium, such as Ringer’s solution or Hartmann’s solution, because a precipitate can form. Precipitation of ceftriaxone-calcium can also occur when ceftriaxone is mixed with calcium-containing solutions in the same IV administration line. Ceftriaxone must not be administered simultaneously with calcium-containing IV solutions, including continuous calcium-containing infusions such as parenteral nutrition via a Y-site. However, in patients other than neonates, ceftriaxone and calcium-containing solutions may be administered sequentially of one another if the infusion lines are thoroughly flushed between infusions with a compatible fluid (see WARNINGS).

There have been no reports of an interaction between ceftriaxone and oral calcium-containing products.

Neonates

Hyperbilirubinemic neonates, especially prematures, should not be treated with Ceftriaxone Injection (see CONTRAINDICATIONS).

Ceftriaxone is contraindicated in neonates if they require (or are expected to require) treatment with calcium-containing IV solutions, including continuous calcium-containing infusions such as parenteral nutrition because of the risk of precipitation of ceftriaxone-calcium (see CONTRAINDICATIONS).

Pediatric Patients

For the treatment of skin and skin structure infections, the recommended total daily dose is 50 to 75 mg/kg given once a day (or in equally divided doses twice a day). The total daily dose should not exceed 2 grams.

For the treatment of serious miscellaneous infections other than meningitis, the recommended total daily dose is 50 to 75 mg/kg, given in divided doses every 12 hours. The total daily dose should not exceed 2 grams.

In the treatment of meningitis, it is recommended that the initial therapeutic dose be 100 mg/kg (not to exceed 4 grams). Thereafter, a total daily dose of 100 mg/kg/day (not to exceed 4 grams daily) is recommended. The daily dose may be administered once a day (or in equally divided doses every 12 hours). The usual duration of therapy is 7 to 14 days.

Adults

The usual adult daily dose is 1 to 2 grams given once a day (or in equally divided doses twice a day) depending on the type and severity of infection. For infections caused by Staphylococcus aureus (MSSA), the recommended daily dose is 2 to 4 grams, in order to achieve >90% target attainment. The total daily dose should not exceed 4 grams.

If Chlamydia trachomatis is a suspected pathogen, appropriate antichlamydial coverage should be added, because ceftriaxone sodium has no activity against this organism.

For preoperative use (surgical prophylaxis), a single dose of 1 gram administered intravenously 1/2 to 2 hours before surgery is recommended.

Generally, Ceftriaxone Injection therapy should be continued for at least 2 days after the signs and symptoms of infection have disappeared. The usual duration of therapy is 4 to 14 days; in complicated infections, longer therapy may be required.

When treating infections caused by Streptococcus pyogenes, therapy should be continued for at least 10 days.

No dosage adjustment is necessary for patients with impairment of hepatic impairment or mild to moderate renal impairment.

DIRECTIONS FOR USE

Ceftriaxone Injection is for intravenous administration using sterile equipment. It should be administered intravenously by infusion over a period of 30 minutes.

Do not add supplementary medication. Vancomycin, amsacrine, aminoglycosides, and fluconazole are physically incompatible with ceftriaxone in admixtures. When any of these drugs are to be administered concomitantly with ceftriaxone by intermittent intravenous infusion, it is recommended that they be given sequentially, with thorough flushing of the intravenous lines (with one of the compatible fluids) between the administrations.

Storage

Store in a freezer capable of maintaining a temperature of -20°C/-4°F.

Thawing of Plastic Container

Thaw frozen container at room temperature (25°C/77°F) or under refrigeration (5°C/41°F). [DO NOT FORCE THAW BY IMMERSION IN WATER BATHS OR BY MICROWAVE IRRADIATION.]

Check for minute leaks by squeezing container firmly. If leaks are detected, discard solution as sterility may be impaired.

Do not add supplementary medication.

Visually inspect the container. If the outlet port protector is damaged, detached, or not present, discard container as solution path sterility may be impaired. Components of the solution may precipitate in the frozen state and will dissolve upon reaching room temperature with little or no agitation. Potency is not affected. Agitate after solution has reached room temperature. If after visual inspection the solution remains cloudy or if an insoluble precipitate is noted, or if any seals are not intact, the container should be discarded.

The thawed solution is stable for 21 days under refrigeration (5°C/41°F) or 48 hours at room temperature (25°C/77°F). Do not refreeze thawed antibiotics.

Caution: Do not use plastic containers in series connections. Such use could result in air embolism due to residual air being drawn from the primary container before administration of the fluid from the secondary container is complete.

Preparation for Intravenous Administration:

1. Suspend container from eyelet support.
2. Remove protector from outlet port at bottom of container.
3. Attach administration set. Refer to complete directions accompanying set.

ANIMAL PHARMACOLOGY

Concretions consisting of the precipitated calcium salt of ceftriaxone have been found in the gallbladder bile of dogs and baboons treated with ceftriaxone.

These appeared as a gritty sediment in dogs that received 100 mg/kg/day for 4 weeks. A similar phenomenon has been observed in baboons but only after a protracted dosing period (6 months) at higher dose levels (335 mg/kg/day or more). The likelihood of this occurrence in humans is considered to be low, since ceftriaxone has a greater plasma half-life in humans, the calcium salt of ceftriaxone is more soluble in human gallbladder bile and the calcium content of human gallbladder bile is relatively low.

HOW SUPPLIED/STORAGE AND HANDLING

Ceftriaxone Injection, USP is supplied premixed as a frozen, iso-osmotic, sterile, nonpyrogenic solution of ceftriaxone sodium in a case of 24 x 50 mL single dose Galaxy containers. The following strengths are available:

1 gm equivalent of ceftriaxone, iso-osmotic with approximately 1.9 gm Dextrose Hydrous, USP, added (NDC 0338-5002-41).

2 gm equivalent of ceftriaxone, iso-osmotic with approximately 1.2 gm Dextrose Hydrous, USP, added (NDC 0338-5003-41).

NOTE: Store Ceftriaxone Injection, USP in the frozen state at or below -20°C/-4°F. See DIRECTIONS FOR USE:

Handle frozen product containers with care. Product containers may be fragile in the frozen state.

Baxter Healthcare Corporation
Deerfield, IL 60015 USA

Printed in USA

Baxter and Galaxy are trademarks of Baxter International Inc. or its subsidiaries.

ATCC is a trademark of the American Type Culture Collection.

07-19-06-950

Rev. September 2024

PACKAGE LABEL - PRINCIPAL DISPLAY PANEL

Container Label 1 g

Container Label 1 g

Baxter
Ceftriaxone
Injection, USP (In Dextrose)

1 g

GALAXY
Single Dose
Container

50 mL
Iso-osmotic

NDC 0338-5002-41
Code 2G3505
Sterile Nonpyrogenic

Each 50 mL contains: Ceftriaxone Sodium, USP equivalent to 1 g ceftriaxone with
approx. 1.9 g Dextrose Hydrous, USP, added to adjust osmolality. pH may have
been adjusted with sodium hydroxide and/or hydrochloric acid. pH range 6.0 to 8.0.

Usual Dosage: See package insert.

Cautions: Administer IV using sterile equipment. Must not be used in series
connections. Do not add supplementary medication. Check for minute leaks and
solution clarity. Rx only.

Store at or below -20°C (-4°F). Thaw at room temperature (25°C/77°F) or
under refrigeration (5°C/41°F). DO NOT FORCE THAW BY IMMERSION
IN WATER BATHS OR BY MICROWAVE IRRADIATION. The thawed solution is stable for 21 days under refrigeration or 48 hours at room temperature. Do not refreeze.

Baxter and GALAXY are trademarks of Baxter International Inc.
Baxter Healthcare Corporation
Deerfield, IL 60015 USA
Made in USA

PL 2040 Plastic

07-34-63-668

*BAR CODE POSITION ONLY
303385002417

Carton Label - 1 g - Panel 1

Carton Label - 1 g - Panel 1

Thaw at room temperature (25°C/77°F) or under refrigeration (5°C/41°F). DO NOT FORCE
THAW BY IMMERSION IN WATER BATHS OR BY MICROWAVE IRRADIATION. The thawed solution is stable for 21 days under refrigeration or 48 hours at room temperature.
Do not refreeze.

Handle frozen product containers with care. Product containers may be fragile in the frozen state.
Baxter and Galaxy are registered trademarks of Baxter International Inc.
PL 2040 Plastic

07-04-65-179

Baxter Logo
Ceftriaxone Injection, USP (In Dextrose)
12 - 50 mL Single-Dose Containers Iso-osmotic
Store at or below -20°C/-4°F. Do not refreeze.

Rx only

1 g
Baxter Healthcare Corporation
Deerfield, IL 60015 USA

Thaw at room temperature (25°C/77°F) or under refrigeration (5°C/41°F). DO NOT FORCE
THAW BYIMMERSION IN WATER BATHS OR BY MICROWAVE IRRADIATION.
The thawed solution is stable for 21 days under refrigeration or 48 hours at room temperature.
Do not refreeze.

Handle frozen product containers with care. Product containers may be fragile in the frozen state.
Baxter and Galaxy are registered trademarks of Baxter International Inc.
PL 2040 Plastic

07-04-65-179

Baxter Logo
Ceftriaxone Injection, USP (In Dextrose)
12 - 50 mL Single-Dose Containers Iso-osmotic
Store at or below -20°C/-4°F. Do not refreeze.

Rx only

1 g
Baxter Healthcare Corporation
Deerfield, IL 60015 USA

Carton Label - 1 g - Panel 2

Carton Label - 1 g - Panel 2

NDC 0338-5002-41
Code 2G3504
*FOR BAR CODE POSITION ONLY
(01) 503385002412

GALAXY Container
Sterile Nonpyrogenic
Each 50 mL contains: Ceftriaxone Sodium, USP equivalent to 1 g ceftriaxone with approx.
1.9 g of Dextrose Hydrous, USP, added to adjust osmolality. pH may have been adjusted with
sodium hydroxide and/or hydrochloric acid. pH range 6.0 to 8.0.

Usual dosage: See package insert.

Cautions: Administer IV using sterile equipment. Must not be used in series connections.
Do not add supplementary medication. Check for minute leaks by squeezing thawed bag firmly. If leaks are found, discard bag as sterility may be impaired. Do not use unless solution is clear.

NDC 0338-5002-41
Code 2G3504
*FOR BAR CODE POSITION ONLY
(01) 503385002412

GALAXY Container
Sterile Nonpyrogenic
Each 50 mL contains: Ceftriaxone Sodium, USP equivalent to 1 g ceftriaxone with approx.
1.9 g of Dextrose Hydrous, USP, added to adjust osmolality. pH may have been adjusted with
sodium hydroxide and/or hydrochloric acid. pH range 6.0 to 8.0.

Usual dosage: See package insert.

Cautions: Administer IV using sterile equipment. Must not be used in series connections.
Do not add supplementary medication. Check for minute leaks by squeezing thawed bag firmly. If leaks are found, discard bag as sterility may be impaired. Do not use unless solution is clear.

Baxter Logo
Ceftriaxone
Injection, USP (In Dextrose)
2 g

GALAXY
Single Dose
Container

50 mL
Iso-osmotic

NDC 0338-5003-41
Code 2G3505
Sterile Nonpyrogenic

Each 50 mL contains: Ceftriaxone Sodium, USP equivalent to 2 g ceftriaxone with
approx. 1.2 g of Dextrose Hydrous, USP, added to adjust osmolality. pH may have
been adjusted with sodium hydroxide and/or hydrochloric acid. pH range 6.0 to 8.0.

Usual dosage: See package insert.

Cautions: Administer IV using sterile equipment. Must not be used in series
connections. Do not add supplementary medication. Check for minute leaks and
solution clarity. Rx only.

Store at or below -20°C (-4°F). Thaw at room temperature (25°C/77°F) or under
refrigeration (5°C/41°F). DO NOT FORCE THAW BY IMMERSION IN WATER
BATHS OR BY MICROWAVE IRRADIATION. The thawed solution is stable for 21 days
under refrigeration or 48 hours at room temperature. Do not refreeze.

Baxter and GALAXY are trademarks of
Baxter International Inc.
Baxter Healthcare Corporation
Deerfield, IL 60015 USA
Made in USA

PL 2040 Plastic

07-34-63-670

*BAR CODE POSITION ONLY
303385003414

Carton Label - 2 g - Panel 1

Carton Label - 2 g - Panel 1

Thaw at room temperature (25°C/77°F) or under refrigeration (5°C/41°F). DO NOT FORCE
THAW BYIMMERSION IN WATER BATHS OR BY MICROWAVE IRRADIATION.
The thawed solution is stable for 21 days under refrigeration or 48 hours at room temperature.
Do not refreeze.
Handle frozen product containers with care. Product containers may be fragile in the frozen state.
Baxter and Galaxy are registered trademarks of Baxter International Inc.
PL 2040 Plastic

07-04-65-180

Baxter Logo
Ceftriaxone Injection, USP (In Dextrose)
12 - 50 mL Single-Dose Containers Iso-osmotic
Store at or below -20°C/-4°F. Do not refreeze.

Rx only

2 g

Baxter Healthcare Corporation
Deerfield, IL 60015 USA

Thaw at room temperature (25°C/77°F) or under refrigeration (5°C/41°F). DO NOT FORCE
THAW BYIMMERSION IN WATER BATHS OR BY MICROWAVE IRRADIATION.
The thawed solution is stable for 21 days under refrigeration or 48 hours at room temperature.
Do not refreeze.
Handle frozen product containers with care. Product containers may be fragile in the frozen state.
Baxter and Galaxy are registered trademarks of Baxter International Inc.
PL 2040 Plastic

07-04-65-180

Baxter Logo
Ceftriaxone Injection, USP (In Dextrose)
12 - 50 mL Single-Dose Containers Iso-osmotic
Store at or below -20°C/-4°F. Do not refreeze.

Rx only

2 g

Baxter Healthcare Corporation
Deerfield, IL 60015 USA

Carton Label - 2 g - Panel 2

Carton Label - 2 g - Panel 2

NDC 0338-5003-41
Code 2G3505
*FOR BAR CODE POSITION ONLY
(01) 503385003419

GALAXY Container
Sterile Nonpyrogenic
Each 50 mL contains: Ceftriaxone Sodium, USP equivalent to 2 g ceftriaxone with approx.
1.2 g of Dextrose Hydrous, USP, added to adjust osmolality. pH may have been adjusted with
sodium hydroxide and/or hydrochloric acid. pH range 6.0 to 8.0.

Usual dosage: See package insert.

Cautions: Administer IV using sterile equipment. Must not be used in series connections.
Do not add supplementary medication. Check for minute leaks by squeezing thawed bag firmly. If leaks are found, discard bag as sterility may be impaired. Do not use unless solution is clear.

NDC 0338-5003-41
Code 2G3505
*FOR BAR CODE POSITION ONLY
(01) 503385003419

GALAXY Container
Sterile Nonpyrogenic
Each 50 mL contains: Ceftriaxone Sodium, USP equivalent to 2 g ceftriaxone with approx.
1.2 g of Dextrose Hydrous, USP, added to adjust osmolality. pH may have been adjusted with
sodium hydroxide and/or hydrochloric acid. pH range 6.0 to 8.0.

Usual dosage: See package insert.

Cautions: Administer IV using sterile equipment. Must not be used in series connections.
Do not add supplementary medication. Check for minute leaks by squeezing thawed bag firmly. If leaks are found, discard bag as sterility may be impaired. Do not use unless solution is clear.